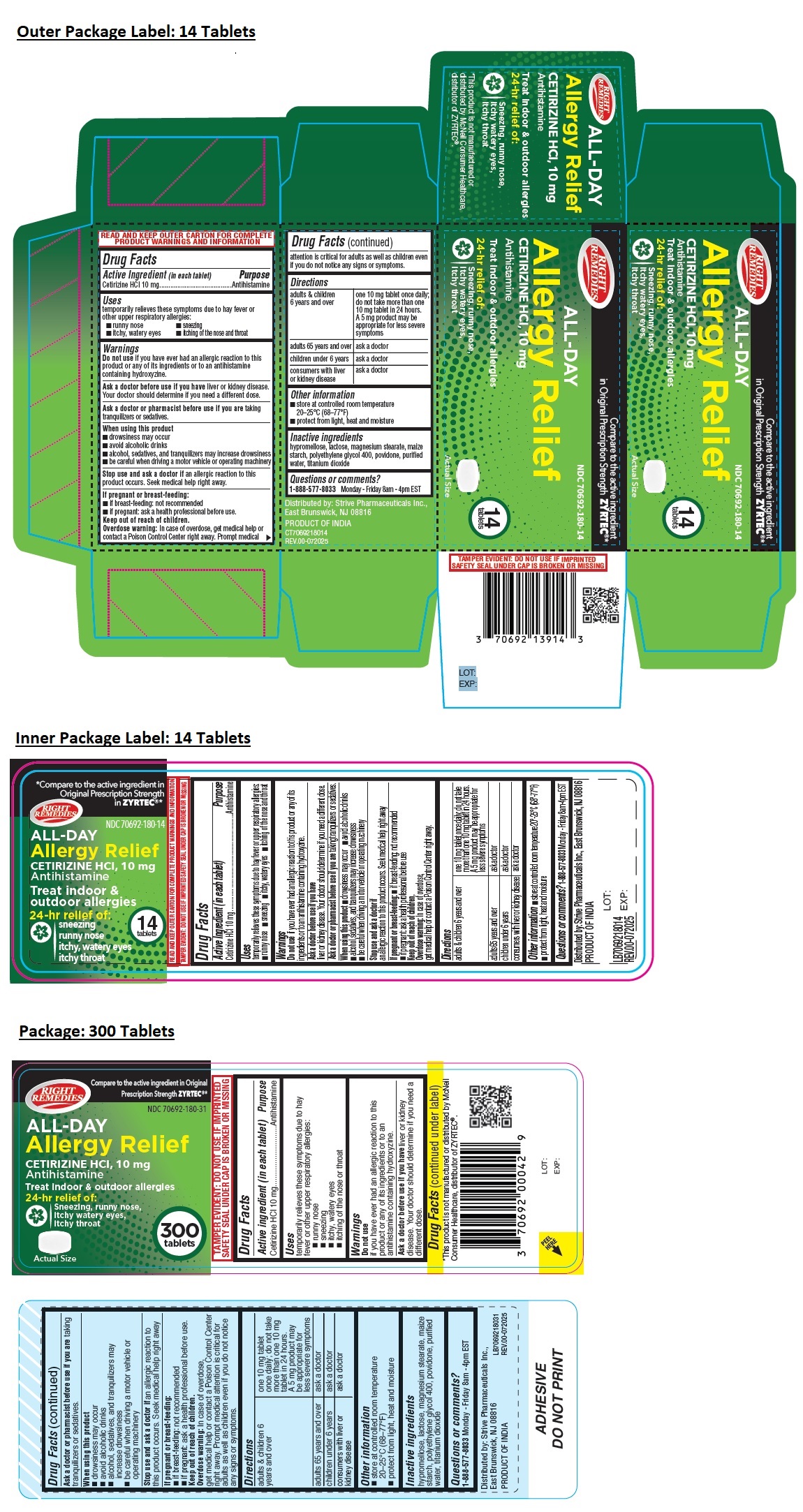 DRUG LABEL: RIGHT REMEDIES ALL-DAY Allergy Relief
NDC: 70692-180 | Form: TABLET, FILM COATED
Manufacturer: Strive Pharmaceuticals Inc.
Category: otc | Type: HUMAN OTC DRUG LABEL
Date: 20251120

ACTIVE INGREDIENTS: CETIRIZINE HYDROCHLORIDE 10 mg/1 1
INACTIVE INGREDIENTS: HYPROMELLOSE, UNSPECIFIED; LACTOSE, UNSPECIFIED FORM; MAGNESIUM STEARATE; STARCH, CORN; POLYETHYLENE GLYCOL 400; POVIDONE, UNSPECIFIED; WATER; TITANIUM DIOXIDE

RIGHT REMEDIES ALL-DAY Allergy Relief

Active Ingredient (in each tablet)

Cetirizine HCl 10 mg

Purpose

Antihistamine

Uses

temporarily relieves these symptoms due to hay fever or other upper respiratory allergies:
• runny nose • sneezing
• itchy, watery eyes • itching of the nose and throat

Warnings

Do not use if you have ever had an allergic reaction to this product or any of its ingredients or to an antihistamine containing hydroxyzine.

Ask a doctor before use if you have liver or kidney disease. Your doctor should determine if you need a different dose.

Ask a doctor or pharmacist before use if you are taking tranquilizers or sedatives.

When using this product
• drowsiness may occur
• avoid alcoholic drinks
• alcohol, sedatives, and tranquilizers may increase drowsiness
• be careful when driving a motor vehicle or operating machinery

Stop use and ask a doctor if an allergic reaction to this product occurs. Seek medical help right away.

If pregnant or breast-feeding:
• if breast-feeding: not recommended
• if pregnant: ask a health professional before use.

Keep out of reach of children.
Overdose warning: In case of overdose, get medical help or contact a Poison Control Center right away. Prompt medical attention is critical for adults as well as children even if you do not notice any signs or symptoms.

Directions

adults & children 6 years and over | one 10 mg tablet once daily; do not take more than one 10 mg tablet in 24 hours. A 5 mg product may be appropriate for less severe symptoms
adults 65 years and over | ask a doctor
children under 6 years | ask a doctor
consumers with liver or kidney disease | ask a doctor

Other information

• store at controlled room temperature 20°–25°C (68°-77°F)
• protect from light, heat and moisture

Inactive ingredients

hypromellose, lactose, magnesium stearate, maize starch, polyethylene glycol 400, povidone, purified water, titanium dioxide

Questions or comments?

1-888-577-8033 Monday - Friday 8am - 4pm EST

Compare to the active ingredient
in Original Prescription Strength ZYRTEC®*

Treat indoor & outdoor allergies

24-hr relief of:
Sneezing, runny nose,
itchy watery eyes,
itchy throat

READ AND KEEP OUTER CARTON FOR COMPLETE PRODUCT WARNINGS AND INFORMATION

Distributed by: Strive Pharmaceuticals Inc.,
East Brunswick, NJ 08816

PRODUCT OF INDIA

*This product is not manufactured or distributed by McNeil Consumer Healthcare, distributor of ZYRTEC®.

TAMPER EVIDENT: DO NOT USE IF IMPRINTED SAFETY SEAL UNDER CAP IS BROKEN OR MISSING

LOT:
EXP: